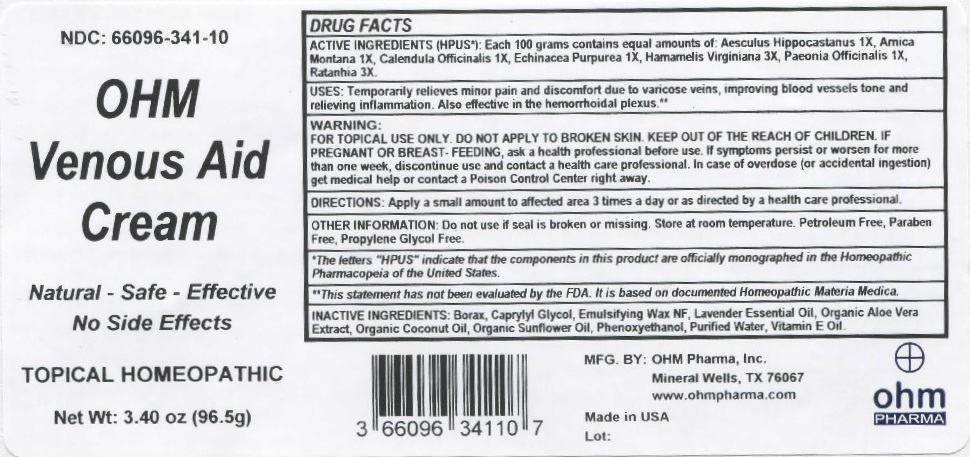 DRUG LABEL: OHM Venous Aid
NDC: 66096-341 | Form: CREAM
Manufacturer: OHM PHARMA INC.
Category: homeopathic | Type: HUMAN PRESCRIPTION DRUG LABEL
Date: 20211229

ACTIVE INGREDIENTS: HORSE CHESTNUT 1 [hp_X]/96.5 g; ARNICA MONTANA 1 [hp_X]/96.5 g; CALENDULA OFFICINALIS FLOWERING TOP 1 [hp_X]/96.5 g; ECHINACEA PURPUREA 1 [hp_X]/96.5 g; HAMAMELIS VIRGINIANA ROOT BARK/STEM BARK 3 [hp_X]/96.5 g; PAEONIA OFFICINALIS ROOT 1 [hp_X]/96.5 g; KRAMERIA LAPPACEA ROOT 3 [hp_X]/96.5 g
INACTIVE INGREDIENTS: SODIUM BORATE; CAPRYLYL GLYCOL; POLYSORBATE 60; LAVENDER OIL; ALOE VERA LEAF; COCONUT OIL; SUNFLOWER OIL; PHENOXYETHANOL; WATER; .ALPHA.-TOCOPHEROL

OHM Venous Aid Cream

ACTIVE INGREDIENT

ACTIVE INGREDIENTS (HPUS*): Each 100 grams contains equal amounts of: Aesculus Hippocastanum 1X, Arnica Montana 1X, Calendula Officinalis 1X, Echinacea Purpurea 1X, Hamamelis Virginiana 3X, Paeonia Officinalis 1X, Ratanhia 3X.

*The letters "HPUS" indicate that the components in this product are officially monographed in the Homeopathic Pharmacopeia of the United STates.

INDICATIONS AND USAGE

USES: Temporarily relieves minor pain and discomfort due to varicose veins, improving blood vessels tone and relieving inflammation. Also effective in the hemorrhoidal plexus.**

**This statement has not been evaluated by the FDA. It is based on documented Homeopathic Materia Medica.

WARNINGS

WARNING: FOR TOPICAL USE ONLY. DO NOT APPLY TO BROKEN SKIN. IF PREGNANT OR BREAST-FEEDING, ask a health professional before use. If symptoms worsen or persist for more than one week, discontinue use and contact a health care professional. In case of overdose (or accidental ingestion) get medical help or contact a Poison Control Center right away.

- KEEP OUT OF REACH OF CHILDREN.

Do not use if seal is broken or missing. Store at room temperature. Petroleum Free, Paraben Free, Propylene Glycol Free.

INACTIVE INGREDIENT

INACTIVE INGREDIENTS: Borax, Caprylyl Glycol, Emulsifying Wax NF, Lavender Essential Oil, Organic Aloe Vera Extract, Organic Coconut Oil, Organic Sunflower Oil, Phenoxyethanol, Purified Water, Vitamin E Oil.

QUESTIONS

MFG. BY: OHM Pharma, Inc. Mineral Wells, TX 76067

www.ohmpharma.com

PACKAGE LABEL

NDC: 66096-341-10

OHM Venous Aid Cream

Natural - Safe - Effective

No Side Effects

TOPICAL HOMEOPATHIC

Net Wt: 3.40oz (96.5g)

Made in USA

PURPOSE

Relieves minor pain.